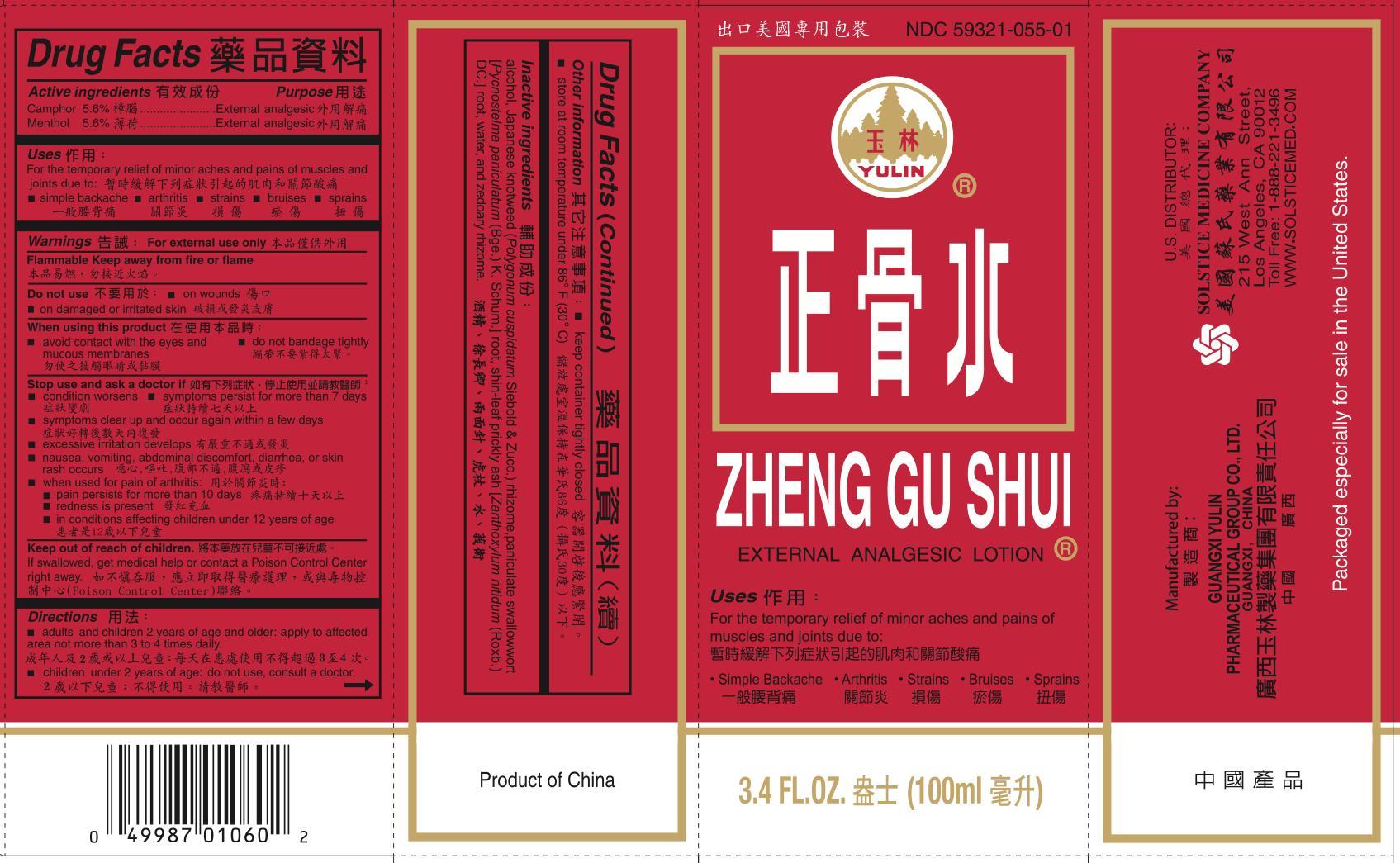 DRUG LABEL: ZHENG GU SHUI
NDC: 59321-055 | Form: LINIMENT
Manufacturer: GUANGXI YULIN PHARMACEUTICAL GROUP CO LTD
Category: otc | Type: HUMAN OTC DRUG LABEL
Date: 20251112

ACTIVE INGREDIENTS: CAMPHOR (SYNTHETIC) 5.6 g/100 mL; MENTHOL 5.6 g/100 mL
INACTIVE INGREDIENTS: ZANTHOXYLUM NITIDUM ROOT; ALCOHOL; POLYGONUM CUSPIDATUM WHOLE; CYNANCHUM PANICULATUM ROOT; WATER; ZEDOARY

DRUG FACTS

Active Ingredients
Camphor 5.6%
Menthol 5.6%

Purpose
External Analgesic
External Analgesic

Uses
For the temporary relief of minor aches and pains of muscles and joints due to:
■ arthritis
■ strains
■ bruises
■ sprains
■ simple backache

Warnings

For external use only

Flammable
Keep away from fire or flame

When using this product
■ avoid contact with the eyes or mucous membranes
■ do not bandage tightly

Stop use and ask a doctor if
■ condition worsens symptoms persist for more than 7 days
■ symptoms clear up and occur again within a few days
■ excessive irritation develops
■ nausea, vomiting, abdominal discomfort, diarrhea, or skin rash occurs
■ when using for pain of arthritis:
■ pain persists for more than 10 days
■ redness is present
■ in conditions affecting children under 12 years of age

KEEP OUT OF REACH OF CHILDREN

Keep out of reach of childrento avoid accidental poisoning.

If swallowed, get medical hep or contact a Poison Control Center right away.

ADVERSE REACTIONS

Report any unexpected side effectsfrom the use of this product to the FDA MedWatch Program.

Directions
■ Adults and children 2 years of age and older: Apply to affected area not more than 3 to 4 times daily.
■ Children under 2 years of age: do no use or consult a doctor.

Other information

■ keep container tightly closed
■ store at room temperature under 86°F (30°C)

Inactive Ingredients
Alcohol, Japanese knotweed (Polygonum cuspidatum Siebold & Zucc.) rhizome, paniculate swallowwort [Pycnostelma paniculatum (Bge.) K. Schum.] root, shin-leaf prickly ash [Zanthoxylum nitidum (Roxb.) DC.] root, water, zedoary rhizome.

Questions or Comments? (888) 221-3496M-F 9 am to 5 pm

PACKAGE LABEL

ZHENG GU SHUI

NDC 59321-055-01

EXTERNAL ANALGESIC LOTION

3.4 FL OZ (100 mL)